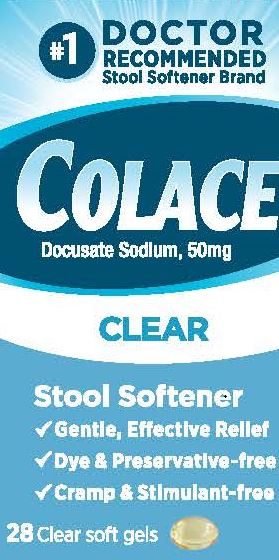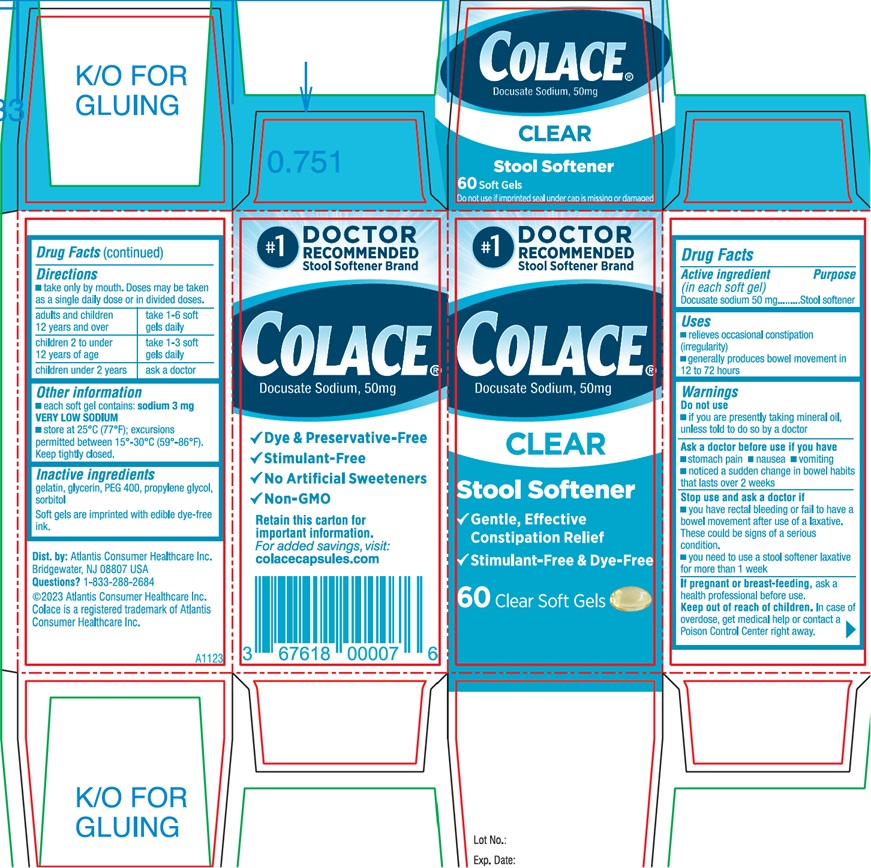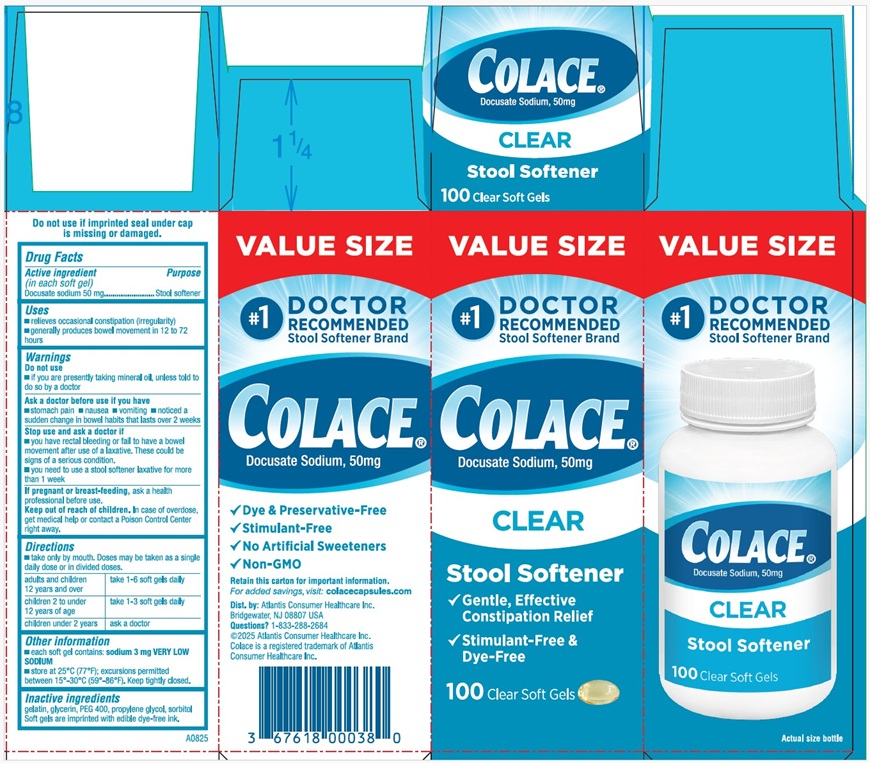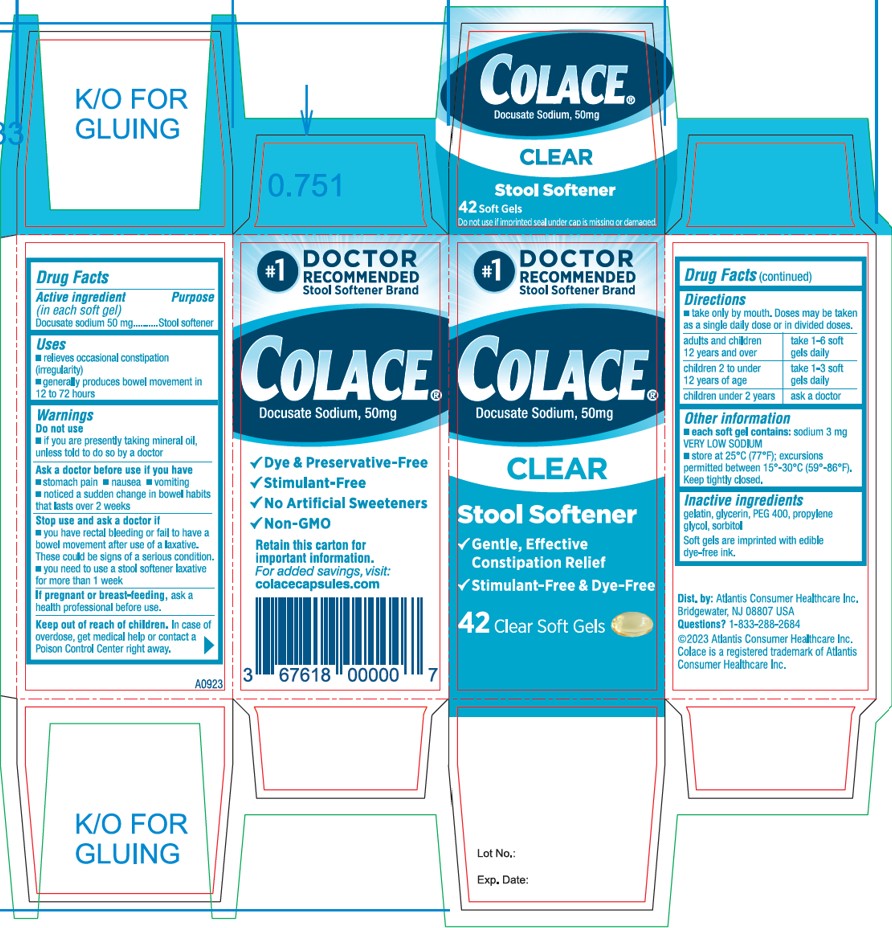 DRUG LABEL: Colace
NDC: 67618-111 | Form: CAPSULE, LIQUID FILLED
Manufacturer: Atlantis Consumer Healthcare, Inc.
Category: otc | Type: HUMAN OTC DRUG LABEL
Date: 20250917

ACTIVE INGREDIENTS: DOCUSATE SODIUM 50 mg/1 1
INACTIVE INGREDIENTS: GELATIN, UNSPECIFIED; GLYCERIN; POLYETHYLENE GLYCOL 400; PROPYLENE GLYCOL; SORBITOL

Colace Clear

Drug Facts

Active ingredient | Purpose
(in each soft gel)
Docusate sodium 50 mg........... | Stool softener

Uses

- relieves occasional constipation (irregularity)
- generally produces bowel movement in 12 to 72 hours

Warnings

Do not use

- if you are presently taking mineral oil, unless told to do so by a doctor

Ask a doctor before use if you have

- stomach pain
- nausea
- vomiting
- noticed a sudden change in bowel habits that lasts over 2 weeks

Stop use and ask a doctor if

- you have rectal bleeding or fail to have a bowel movementafter use of a laxative. These could be signs of a serious condition.
- you need to use a stool softener laxative for more than1 week

PREGNANCY OR BREAST FEEDING

If pregnant or breast-feeding, ask a health professional before use.

Keep out of reach of children. In case of overdose, get medical help or contact a Poison Control Center right away.

Directions

- Take only by mouth. Doses may be taken as a single daily dose or in divided doses.

adults and children 12 years and over | take 1-6 soft gels daily
children 2 to under 12 years of age | take 1-3 soft gels daily
children under 2 years | ask a doctor

Other information

- each soft gel contains: sodium 3 mg VERY LOW SODIUM
- store at 25°C (77°F); excursions permitted between 15°-30°C (59°-86°F).

Keep tightly closed.

Inactive ingredients
gelatin, glycerin, PEG 400, propylene glycol, sorbitol

Soft gels are imprinted with edible dye-free ink.

Dist. by: Atlantis Consumer Healthcare Inc.
Bridgewater, NJ 08807
Questions? 1-833-288-2684
©2023 Atlantis Consumer Healthcare Inc.
Colace is a registered trademark of Atlantis Consumer Healthcare Inc.

PACKAGE LABEL.PRINCIPAL DISPLAY PANEL

#1 DOCTOR
RECOMMENDED
Stool Softener Brand
Colace
Docusate Sodium, 50mg
CLEAR
Stool Softener
√ Gentle, Effective Relief
√ Dye & Preservative-free
√ Cramp & Stimulant-free
28 Clear Soft Gels

Front Panel
#1 DOCTOR
RECOMMENDED
Stool Softener Brand
Colace®
Docusate Sodium, 50mg
CLEAR
Stool Softener
√ Gentle, Effective
Constipation Relief
√ Stimulant-Free & Dye-Free
42 Clear Soft Gels
Side Panel
Colace®
Docusate Sodium, 50mg
√ Dye & Preservative-Free
√ Stimulant-Free
√ No Artificial Sweeteners
√ Non-GMO
Retain this carton for
Important information.
For added savings, visit:
colacecapsules.com
Dist. by: Atlantis Consumer Healthcare Inc.
Bridgewater, NJ 08807 USA
Questions? 1-833-288-2684
©2023 Atlantis Consumer Healthcare Inc.
Colace is a registered trademark of Atlantis
Consumer Healthcare Inc.
Lot No.:
Exp. Date:
A0923

Front Panel
#1 DOCTOR
RECOMMENDED
Stool Softener Brand
Colace®
Docusate Sodium, 50mg
CLEAR
Stool Softener
√ Gentle, Effective
Constipation Relief
√ Stimulant-Free & Dye-Free
60 Clear Soft Gels
Side Panel
Colace®
Docusate Sodium, 50mg
√ Dye & Preservative-Free
√ Stimulant-Free
√ No Artificial Sweeteners
√ Non-GMO
Retain this carton for
Important information.
For added savings, visit:
colacecapsules.com
Dist. by: Atlantis Consumer Healthcare Inc.
Bridgewater, NJ 08807 USA
Questions? 1-833-288-2684
©2023 Atlantis Consumer Healthcare Inc.
Colace is a registered trademark of Atlantis
Consumer Healthcare Inc.
Lot No.:
Exp. Date:
A1123

Front Panel
VALUE SIZE
#1 DOCTOR
RECOMMENDED
Stool Softener Brand
Colace®
Docusate Sodium, 50mg
CLEAR
Stool Softener
√ Gentle, Effective
Constipation Relief
√ Stimulant-Free & Dye-Free
100 Clear Soft Gels
Side Panel
Colace®
Docusate Sodium, 50mg
√ Dye & Preservative-Free
√ Stimulant-Free
√ No Artificial Sweeteners
√ Non-GMO
Retain this carton for Important information.
For added savings, visit: colacecapsules.com
Dist. by: Atlantis Consumer Healthcare Inc.
Bridgewater, NJ 08807 USA
Questions? 1-833-288-2684
©2025 Atlantis Consumer Healthcare Inc.
Colace is a registered trademark of Atlantis
Consumer Healthcare Inc.
Lot No.:
Exp. Date:
A0825